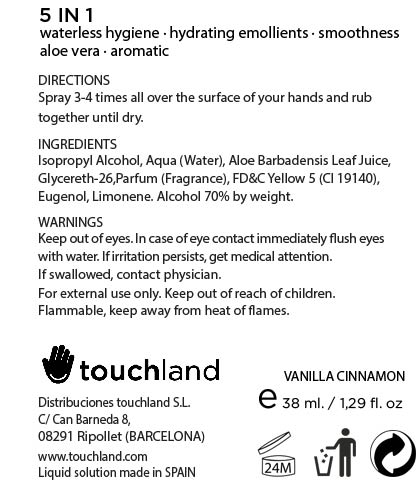 DRUG LABEL: TOUCHLAND kub2go Hand Sanitizer Vanilla
NDC: 70083-008 | Form: LIQUID
Manufacturer: Distribuciones Touchland S.L.
Category: otc | Type: HUMAN OTC DRUG LABEL
Date: 20150921

ACTIVE INGREDIENTS: ISOPROPYL ALCOHOL 0.7 mL/1 mL
INACTIVE INGREDIENTS: WATER; ALOE VERA LEAF; GLYCERETH-26; FD&C YELLOW NO. 5; EUGENOL; LIMONENE, (+)-

Active ingredient

Isopropyl alcohol 70% (W/W)

Directions

Spray 3-4 times all over the surface of your hands and rub together until dry. Supervise children in the use of this product.

Inactive ingredients

Aqua (Water), Aloe Barbadensis Leaf Juice, Glycereth-26, Parfum (Fragrance), FD&C Yellow 5 (CI 19140), Eugenol, Limonene.

Warnings

Keep out of eyes. In case of eye contact immediately flush eyes with water. If irritation persists, get medical attention. If swallowed, contact physician.

For external use only. Keep out of reach of children.

Flammable, keep away from heat of flames.

Uses

Kills 99.99% of all disease causing germs on contact, and protects and restores moisture.

Purpose

Antiseptic